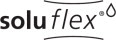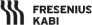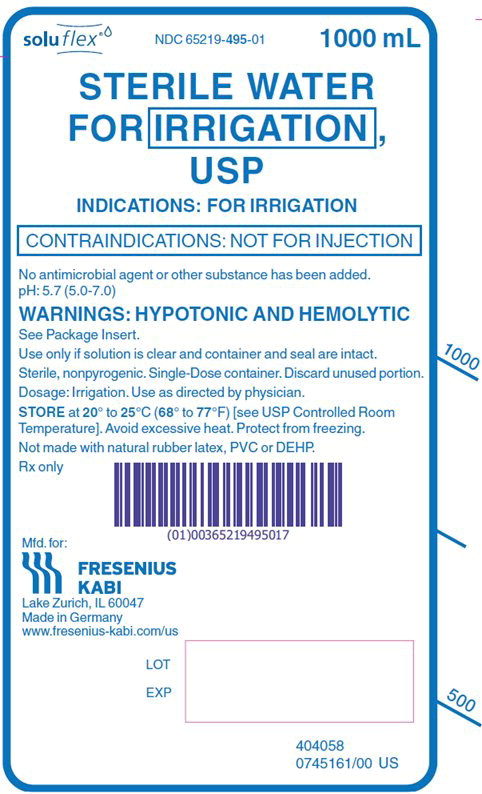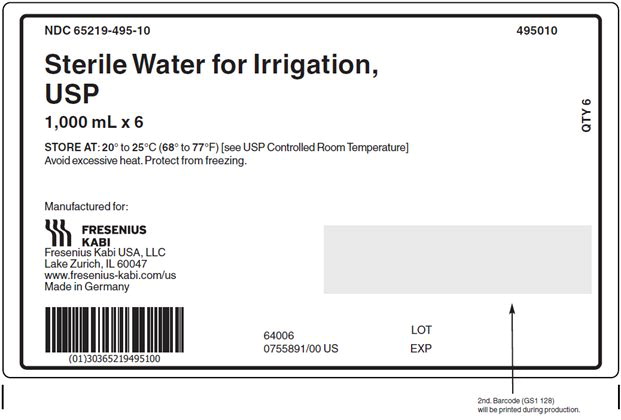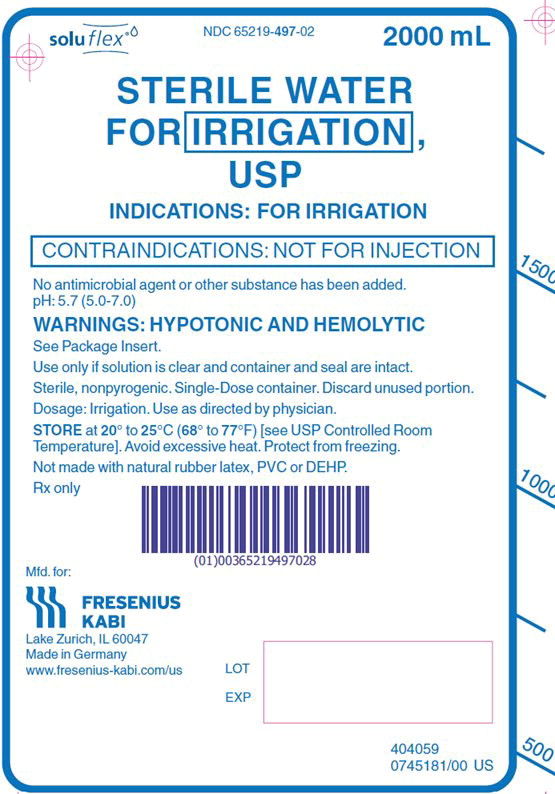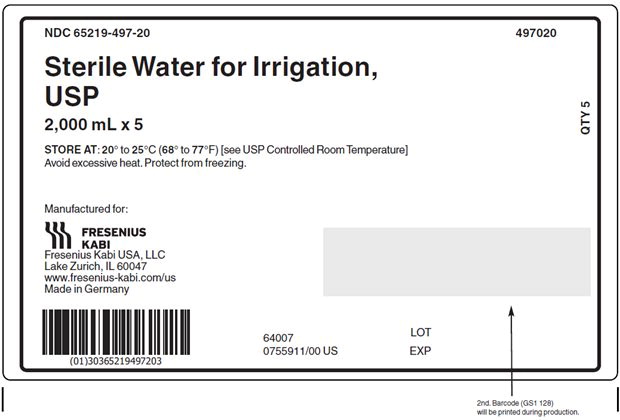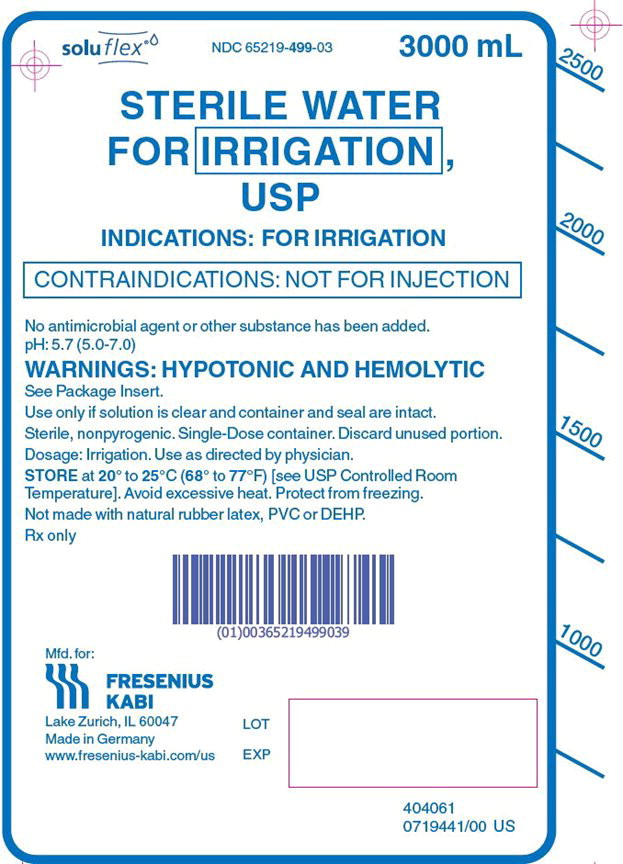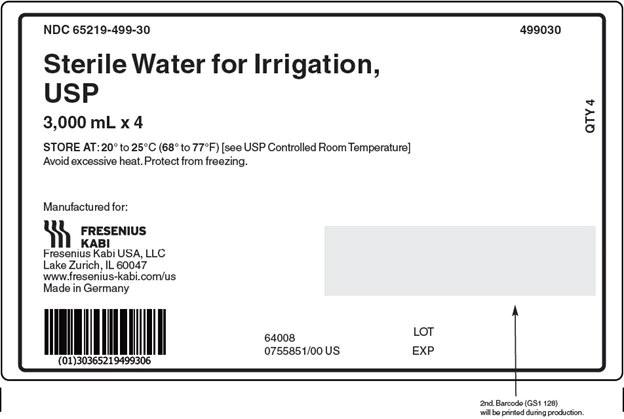 DRUG LABEL: Sterile Water
NDC: 65219-495 | Form: INJECTION
Manufacturer: Fresenius Kabi USA, LLC
Category: prescription | Type: HUMAN PRESCRIPTION DRUG LABEL
Date: 20251118

ACTIVE INGREDIENTS: WATER 1 mL/1 mL

Sterile Water for Irrigation, USP

Rx only

DESCRIPTION

Sterile Water for Irrigation, USP is a sterile, hypotonic, nonpyrogenic irrigating fluid or pharmaceutic aid (solvent) entirely composed of Sterile Water for Injection, USP. It is prepared by distillation and contains no antimicrobial or bacteriostatic agents or added buffers.

The pH is 5.7 (5.0-7.0)

The flexible plastic container is made from a multilayered film specifically developed for parenteral drugs. It contains no plasticizers. The solution contact layer is a copolymer of ethylene and propylene. The container is nontoxic and biologically inert. The container-solution unit is a closed system and is not dependent upon entry of external air during administration.

Not made with natural rubber latex, PVC or DEHP.

CLINICAL PHARMACOLOGY

Sterile Water for Irrigation is utilized for a variety of clinical indications. Because of its low refractive index (1.3325), water provides excellent visibility during endoscopic urological procedures. It is also utilized as a pharmaceutic aid, as well as in the preparation of enteral nutrient products.

Water is hypotonic and will cause hemolysis and will be readily absorbed by the tissues during surgical procedures; therefore, its use under such conditions is not recommended.

INDICATIONS AND USAGE

Sterile Water for Irrigation is indicated for use as an irrigating fluid or pharmaceutic aid. Sterile Water may also be used as an adjunct in the preparation of non-intravenously administered nutrient mixtures (see DOSAGE AND ADMINISTRATION).

CONTRAINDICATIONS

Not for injection.

WARNINGS

Sterile Water for Irrigation is hypotonic and will cause hemolysis, and is not recommended for use during surgical procedures.

After opening container, its contents should be used promptly to minimize the possibility of bacterial growth or pyrogen formation.

Discard unused portion of irrigating solution since it contains no preservative.

PRECAUTIONS

Use only if solution is clear and container and seal are intact.

ADVERSE REACTIONS

None known.

To report SUSPECTED ADVERSE REACTIONS, contact Fresenius Kabi USA, LLC at 1-800-551-7176 or FDA at 1-800-FDA-1088 or www.fda.gov/medwatch.

OVERDOSAGE

None known.

DOSAGE AND ADMINISTRATION

Irrigation

Use as directed by physician.

This drug product should be inspected visually for particulate matter and discoloration prior to administration, whenever solution and container permit.

Nutrient Mixtures

Sterile Water for Irrigation, USP may be used to prepare non-intravenously administered nutrient mixtures. It contains no electrolytes or other added substances. Refer to preparation instructions of particular mixture to be used. The plastic container may be used for administration of non-intravenous nutrient mixture to the patient as appropriate.

HOW SUPPLIED

Sterile Water for Irrigation, USP is supplied sterile and nonpyrogenic in single dose flexible plastic containers.

Product Code | Unit of Sale | Each
495010 | NDC 65219-495-10 Package of 6 bags | NDC 65219-495-01 1000 mL fill in a 1500 mL bag
497020 | NDC 65219-497-20 Package of 5 bags | NDC 65219-497-02 2000 mL fill in a 2000 mL bag
499030 | NDC 65219-499-30 Package of 4 bags | NDC 65219-499-03 3000 mL fill in a 3000 mL bag

Exposure of pharmaceutical products to heat should be minimized. Avoid excessive heat. Protect from freezing. Store at 20° to 25°C (68° to 77°F). [see USP Controlled Room Temperature]; however, brief exposure up to 40°C (104°F) does not adversely affect the product.

INSTRUCTIONS FOR USE:

Not for Injection. Not for use with pressurized irrigation systems.

Check solution container composition, lot number, and expiry date.

Irrigation solutions should be inspected visually for particulate matter and discoloration prior to administration, whenever solution and container permit.

Do not use if the solution is cloudy or precipitate is present.

Check the solution container for leaks by squeezing firmly. If leaks are found, discard.

The intact port cap provides visual tamper evidence. Do not use if port cap is prematurely removed. Maintain strict aseptic technique during handling.

To Add Medication:

1. Identify WHITE Additive Port with arrow pointing toward solution container.
2. Immediately before injecting additives, break off WHITE Additive Port Cap with the arrow pointing toward solution container.
3. Hold base of WHITE Additive Port.
4. Insert needle (18 – 23 gauge) through the center of the WHITE Additive Port's resealable septum and inject additives.
5. Mix solution container contents thoroughly.
6. WHITE Additive port must be swabbed with disinfection agent before re-puncturing.
7. Check admixture visually for particulate matter.

Preparation for Administration

1. Immediately before inserting the irrigation set, break off BLUE Administration Port Cap with the arrow pointing away from the solution container.
2. Use non-vented irrigation set or close the air-inlet on a vented set. Refer to directions for use accompanying the irrigation set.
3. Hold the base of the BLUE Administration Port, twist and push spike until fully inserted.
4. The BLUE Administration Port contains a self-sealing septum that helps prevent leakage after removing the spike. The Administration Port is not intended to be spiked more than once.
5. Suspend solution container from hanger hole.
6. For Single Use Only. Discard unused portion.

Manufactured for:

Lake Zurich, IL 60047

Made in Germany
www.fresenius-kabi.com/us

451819
Issued: September 2024

PACKAGE LABEL - PRINCIPAL DISPLAY – Sterile Water for Irrigation, USP 1000 mL Bag Label

soluflex® NDC 65219-495-01 1000 mL

STERILE WATER
FOR IRRIGATION,
USP
INDICATIONS: FOR IRRIGATION

CONTRAINDICATIONS: NOT FOR INJECTION

PACKAGE LABEL - PRINCIPAL DISPLAY - Sterile Water for Irrigation, USP 1000 mL Case Label

NDC 65219-495-10 495010

Sterile Water for Irrigation,
USP
1,000 mL x 6

STORE AT: 20° to 25°C (68° to 77°F) [see USP Controlled Room Temperature]
Avoid excessive heat. Protect from freezing.

PACKAGE LABEL - PRINCIPAL DISPLAY – Sterile Water for Irrigation, USP 2000 mL Bag Label

soluflex® NDC 65219-497-02 2000 mL

STERILE WATER
FOR IRRIGATION,
USP
INDICATIONS: FOR IRRIGATION

CONTRAINDICATIONS: NOT FOR INJECTION

PACKAGE LABEL - PRINCIPAL DISPLAY - Sterile Water for Irrigation, USP 2000 mL Case Label

NDC 65219-497-20 497020

Sterile Water for Irrigation,
USP
2,000 mL x 5

STORE AT: 20° to 25°C (68° to 77°F) [see USP Controlled Room Temperature]
Avoid excessive heat. Protect from freezing.

PACKAGE LABEL - PRINCIPAL DISPLAY – Sterile Water for Irrigation, USP 3000 mL Bag Label

soluflex® NDC 65219-499-03 3000 mL

STERILE WATER
FOR IRRIGATION,
USP
INDICATIONS: FOR IRRIGATION

CONTRAINDICATIONS: NOT FOR INJECTION

PACKAGE LABEL - PRINCIPAL DISPLAY - Sterile Water for Irrigation, USP 3000 mL Case Label

NDC 65219-499-30 499030

Sterile Water for Irrigation,
USP
3,000 mL x 4

STORE AT: 20° to 25°C (68° to 77°F) [see USP Controlled Room Temperature]
Avoid excessive heat. Protect from freezing.